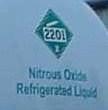 DRUG LABEL: Nitrous Oxide
NDC: 54260-001 | Form: GAS
Manufacturer: Nitrous Oxide
Category: prescription | Type: HUMAN PRESCRIPTION DRUG LABEL
Date: 20251111

ACTIVE INGREDIENTS: NITROUS OXIDE 990 mL/1 L

nitrous oxide

PACKAGE LABEL

Airgas

2201

Nitrous Oxide

Refrigerated Liquid